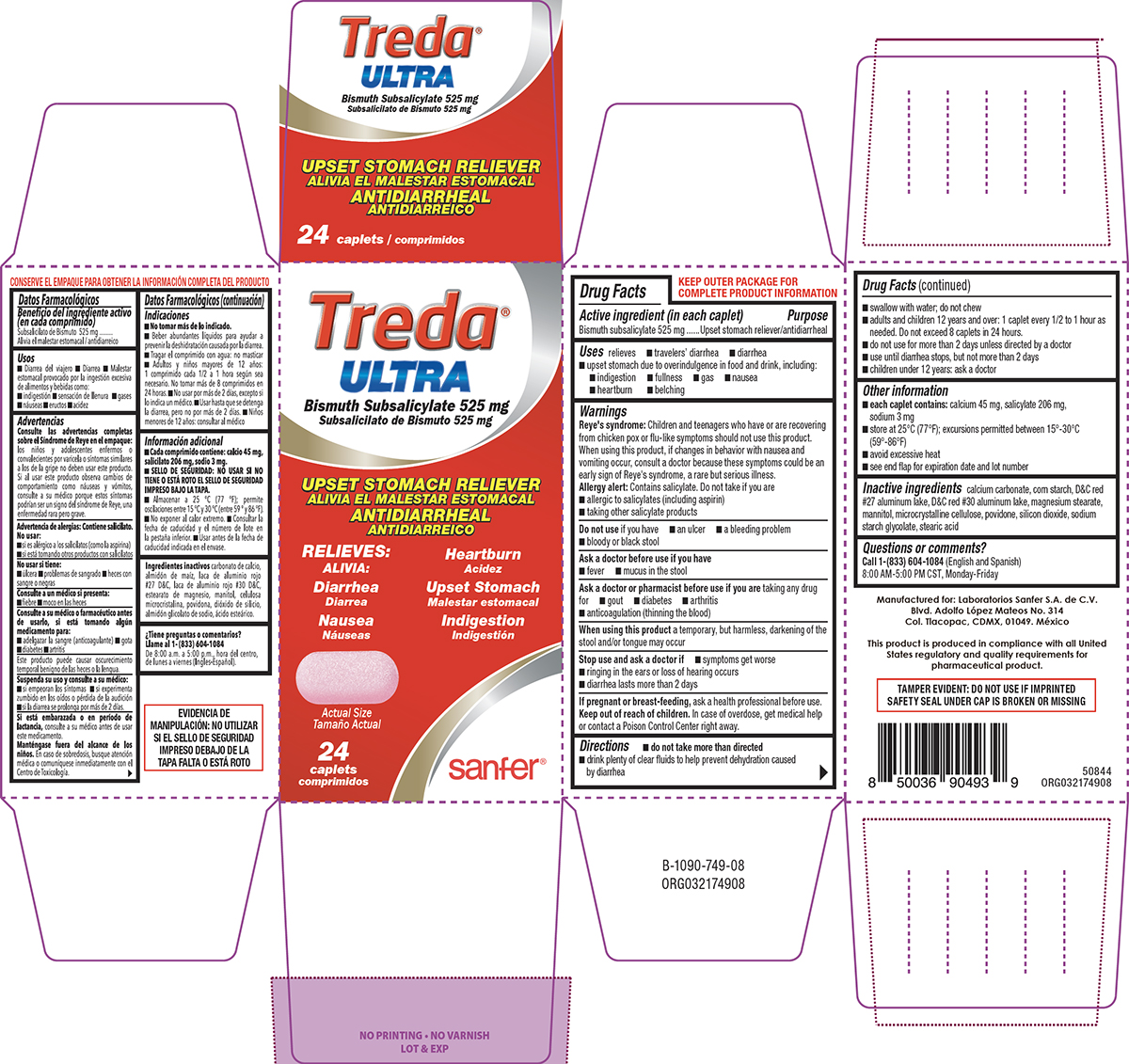 DRUG LABEL: Treda Ultra
NDC: 83393-749 | Form: TABLET
Manufacturer: Laboratorios Sanfer, S.A. de C.V.
Category: otc | Type: HUMAN OTC DRUG LABEL
Date: 20260212

ACTIVE INGREDIENTS: BISMUTH SUBSALICYLATE 525 mg/1 1
INACTIVE INGREDIENTS: CALCIUM CARBONATE; STARCH, CORN; D&C RED NO. 27 ALUMINUM LAKE; D&C RED NO. 30; MAGNESIUM STEARATE; MANNITOL; MICROCRYSTALLINE CELLULOSE; POVIDONE, UNSPECIFIED; SILICON DIOXIDE; SODIUM STARCH GLYCOLATE TYPE A POTATO; STEARIC ACID

Treda Ultra 44-749

Active ingredient (in each caplet)

Bismuth subsalicylate 525 mg

Purpose

Upset stomach reliever/antidiarrheal

Uses

relieves

- travelers’ diarrhea
- diarrhea
- upset stomach due to overindulgence in food and drink, including:
  - indigestion
  - fullness
  - gas
  - nausea
  - heartburn
  - belching

Warnings

Reye's syndrome: Children and teenagers who have or are recovering from chicken pox or flu-like symptoms should not use this product. When using this product, if changes in behavior with nausea and vomiting occur, consult a doctor because these symptoms could be an early sign of Reye's syndrome, a rare but serious illness.

Allergy alert: Contains salicylate. Do not take if you are

- allergic to salicylates (including aspirin)
- taking other salicylate products

Do not use

if you have

- an ulcer
- a bleeding problem
- bloody or black stool

Ask a doctor before use if you have

- fever
- mucus in the stool

Ask a doctor or pharmacist before use if you are

taking any drug for

- gout
- diabetes
- arthritis
- anticoagulation (thinning the blood)

When using this product

a temporary, but harmless, darkening of the stool and/or tongue may occur

Stop use and ask a doctor if

- symptoms get worse
- ringing in the ears or loss of hearing occurs
- diarrhea lasts more than 2 days

If pregnant or breast-feeding,

ask a health professional before use.

Keep out of reach of children.

In case of overdose, get medical help or contact a Poison Control Center right away.

Directions

- do not take more than directed
- drink plenty of clear fluids to help prevent dehydration caused by diarrhea
- swallow with water; do not chew
- adults and children 12 years and over: 1 caplet every 1/2 to 1 hour as needed. Do not exceed 8 caplets in 24 hours.
- do not use for more than 2 days unless directed by a doctor
- use until diarrhea stops, but not more than 2 days
- children under 12 years: ask a doctor

Other information

- each caplet contains: calcium 45 mg, salicylate 206 mg, sodium 3 mg
- store at 25°C (77°F); excursions permitted between 15°-30°C (59°-86°F)
- avoid excessive heat
- see end flap for expiration date and lot number

Inactive ingredients

calcium carbonate, corn starch, D&C red #27 aluminum lake, D&C red #30 aluminum lake, magnesium stearate, mannitol, microcrystalline cellulose, povidone, silicon dioxide, sodium starch glycolate, stearic acid

Questions or comments?

Call 1-(833) 604-1084 (English and Spanish) 8:00 AM-5:00 PM CST, Monday-Friday

Principal display panel

Treda®
Ultra

Bismuth Subsalicylate 525 mg

UPSET STOMACH RELIEVER
ANTIDIARRHEAL

RELIEVES:

Diarrhea

Nausea

Heartburn

Upset Stomach

Indigestion

Actual Size

24
caplets

sanfer®

TAMPER EVIDENT: DO NOT USE IF IMPRINTED
SAFETY SEAL UNDER CAP IS BROKEN OR MISSING

50844
ORG032174908

Manufactured for: Laboratorios Sanfer S.A. de C.V.
Blvd. Adolfo López Mateos No. 314
Col. Tlacopac, CDMX, 01049. México

This product is produced in compliance with all United
States regulatory and quality requirements for
pharmaceutical product.

Treda Ultra 44-749